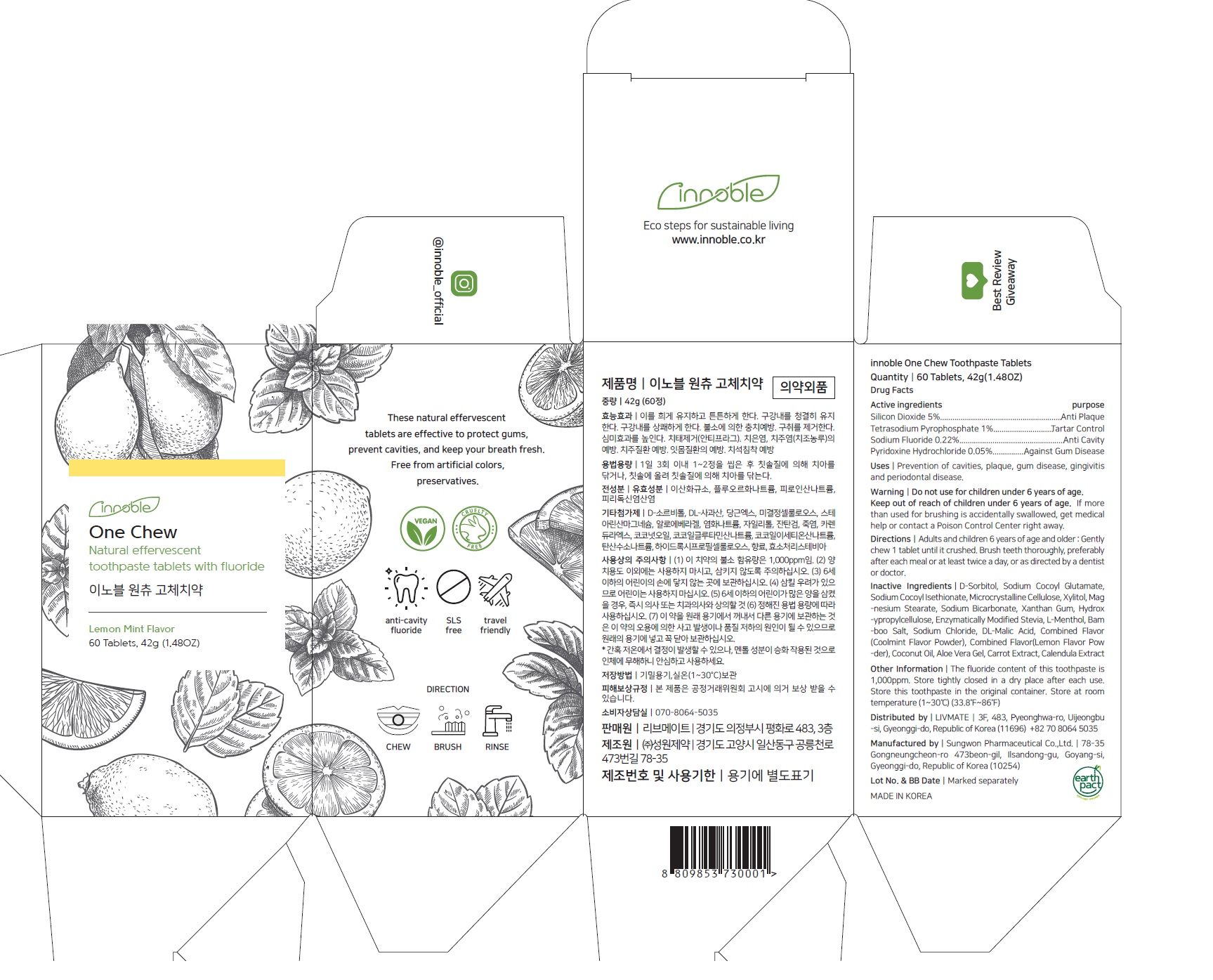 DRUG LABEL: Innoble ONECHEWTOOTHPASTE
NDC: 82709-001 | Form: TABLET
Manufacturer: livmate
Category: otc | Type: HUMAN OTC DRUG LABEL
Date: 20220504

ACTIVE INGREDIENTS: SODIUM FLUORIDE 0.22 g/100 g; SILICON DIOXIDE 5 g/100 g; SODIUM PYROPHOSPHATE 1 g/100 g; PYRIDOXINE HYDROCHLORIDE 0.05 g/100 g
INACTIVE INGREDIENTS: SORBITOL; SODIUM COCOYL GLUTAMATE; SODIUM COCOYL ISETHIONATE; MICROCRYSTALLINE CELLULOSE; XYLITOL; MAGNESIUM STEARATE; SODIUM BICARBONATE; XANTHAN GUM; HYDROXYPROPYL CELLULOSE, UNSPECIFIED; LEVOMENTHOL; SODIUM CHLORIDE; MALIC ACID; COCONUT OIL; ALOE VERA LEAF; CARROT

ACTIVE INGREDIENT

Silicon Dioxide, Tetrasodium Pyrophosphate, Pyridoxine Hydrochloride, Sodium Fluoride

INACTIVE INGREDIENT

D-Sorbitol, Sodium Cocoyl Glutamate, Sodium Cocoyl Isethionate, Microcrystalline Cellulose, Xylitol, Magnesium Stearate, Sodium Bicarbonate, Xanthan Gum, Hydroxypropylcellulose, Enzymatically Modified Stevia, L-Menthol, Bamboo Salt, Sodium Chloride, DL-Malic Acid, Combined Flavor(Coolmint Flavor Powder), Combined Flavor(Lemon Flavor Powder), Coconut Oil, Aloe Vera Gel, Carrot Extract, Calendula Extract

PURPOSE

Anti plaque

Tartar Control

Anti Cavity

Against gum disease

KEEP OUT OF REACH OF CHILDREN

WARNING

Do not use for children under 6 years of age.

Directions

Adults and children 6 years of age and older; Gently chew 1 tablet until it crushed. Brush teeth thoroughly, preferably after each meal or at least twice a day, or as directed by a dentist or doctor.

INDICATION & USAGE SECTION

Prevention of cavities, plaque, gum disease, gingivitis and periodontal disease.